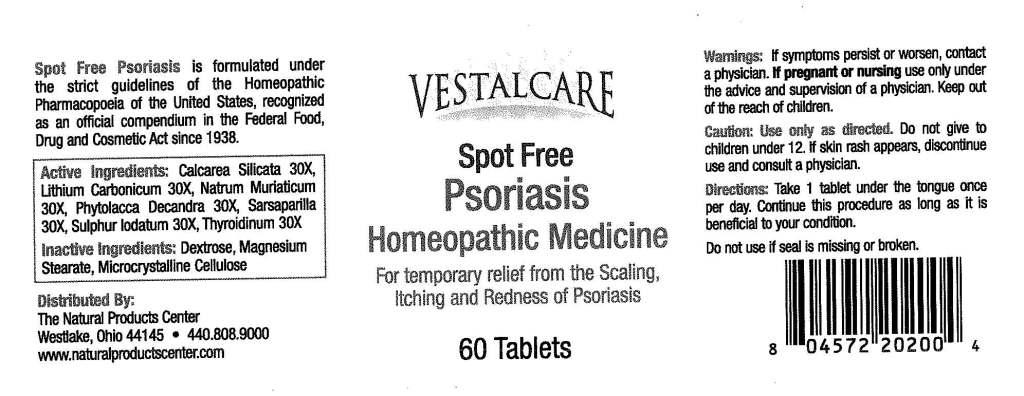 DRUG LABEL: VestalCare Spot Free Psoriasis
NDC: 57520-0598 | Form: TABLET
Manufacturer: Apotheca Company
Category: homeopathic | Type: HUMAN OTC DRUG LABEL
Date: 20110225

ACTIVE INGREDIENTS: CALCIUM SILICATE     30 [hp_X]/1 1; LITHIUM CARBONATE 30 [hp_X]/1 1; SODIUM CHLORIDE 30 [hp_X]/1 1; PHYTOLACCA AMERICANA ROOT 30 [hp_X]/1 1; SARSAPARILLA ROOT 30 [hp_X]/1 1; SULFUR IODIDE 30 [hp_X]/1 1; THYROID 30 [hp_X]/1 1
INACTIVE INGREDIENTS: DEXTROSE; CELLULOSE, MICROCRYSTALLINE; MAGNESIUM STEARATE

VestalCare Spot Free Psoriasis

ACTIVE INGREDIENT

ACTIVE INGREDIENTS: Calcarea silicata 30X, Lithium carbonicum 30X, Natrum muriaticum 30X, Phytolacca decandra 30X, Sarsaparilla 30X, Sulphur iodatum 30X, Throidinum 30X.

PURPOSE

For temporary relief from the Scaling, Itching and Redness of Psoriasis.

WARNINGS

WARNINGS: If symptoms persist or worsen, contact a physician.

If pregnant or nursing use only under the advice and supervision of a physician.

Keep out of the reach of children.

Do not use if seal is missing or broken.

CAUTION: Use only as directed. Do not give to children under 12. If skin rash appears, discontinue use and consult a physician.

DOSAGE AND ADMINISTRATION

DIRECTIONS: Take 1 tablet under the tongue once per day. Continue this procedure as long as it is beneficial to your condition.

INACTIVE INGREDIENT

INACTIVE INGREDIENTS: Destrose, Magnesium stearate, Microcrystalline cellulose.

KEEP OUT OF THE REACH OF CHILDREN.

INDICATIONS AND USAGE

For temporary relief from the Scaling, Itching and Redness of Psoriasis.

QUESTIONS

Distributed By:

The Natural Products Center

Westlake, Ohio 44145

440-808-9000

www.naturalproductscenter.com

PACKAGE LABEL

VESTALCARE

Spot Free Psoriasis

Homeopathic Medicine

For temporary relief from the Scaling, Itching and Redness of Psoriasis

60 Tablets